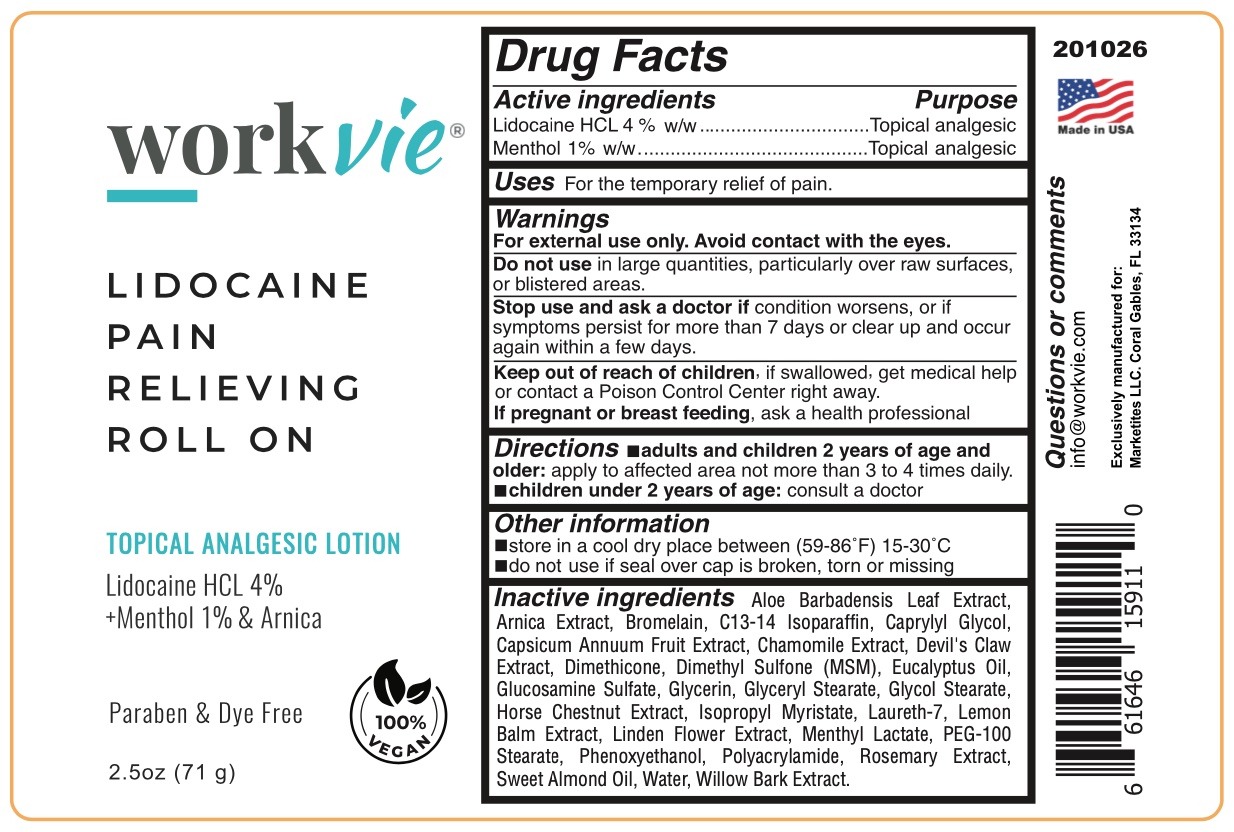 DRUG LABEL: Workvie
NDC: 72393-203 | Form: CREAM
Manufacturer: Marketites LLC
Category: otc | Type: HUMAN OTC DRUG LABEL
Date: 20251029

ACTIVE INGREDIENTS: MENTHOL 1 g/100 g; LIDOCAINE HYDROCHLORIDE 4 g/100 g
INACTIVE INGREDIENTS: GLYCERIN; GLYCOL STEARATE; HORSE CHESTNUT; ISOPROPYL MYRISTATE; PEG-100 STEARATE; ARNICA MONTANA; CAPRYLYL GLYCOL; CHAMOMILE; ROSEMARY OIL; ALOE VERA LEAF; LEMON BALM OIL; LINDEN LEAF; DIMETHYL SULFONE; PHENOXYETHANOL; SALIX NIGRA BARK; EUCALYPTUS GLOBULUS LEAF; GLUCOSAMINE SULFATE POTASSIUM CHLORIDE; GLYCERYL MONOSTEARATE; MENTHYL LACTATE, (-)-; ALMOND OIL; HARPAGOPHYTUM PROCUMBENS ROOT; C13-14 ISOPARAFFIN; FRUIT BROMELAIN; DIMETHICONE; CAPSICUM ANNUUM WHOLE; POLYACRYLAMIDE (10000 MW); LAURETH-7

WKV LidoHCL

Active Ingredients

Lidocaine HCL 4% w/w

Menthol 1% w/w

Purpose

Topical analgesic

Topical analgesic

INDICATIONS AND USAGE

USES For temporary relief of pain.

Warnings

For external use only. Avoid contact with eyes.

Do not use in large quantities, particularly over raw surfaces, or blistered areas.

Stop use and ask a doctor if condition worsens, or if symptoms persist for more than 7 days or clear up and occur again within a few days.

Keep out of reach of children, if swallowed, get medical help or contact a Poison Control Center right away.

If pregnant or breast feeding, ask a health professional.

DOSAGE AND ADMINISTRATION

Directions adults and children 2 years of age and older: apply to affected area not more than 3 to 4 times daily.

Children under 2 years of age: consult a doctor.

Other Information

store in a cool dry place between (59-86°F) 15-30°C

don't use if seal over cap is broken, torn or missing

Inactive Ingredients

Aloe Barbadensis Leaf Extract, Arnica Extract, Bromelain, C13-14 Isoparaffin, Caprylyl Glycol, Capsicum Annuum Fruit Extract, Chamomile Extract, Devil’s Claw Extract, Dimethicone, Dimethyl Sulfone (MSM), Eucalyptus Oil, Glucosamine Sulfate, Glycerin, Glyceryl Stearate, Glycol Stearate, Horse Chestnut Extract, Isopropyl Myristate, Laureth-7, Lemon Balm Extract, Linden Flower Extract, Menthyl Lactate, PEG-100 Stearate, Phenoxyethanol, Polyacrylamide, Rosemary Extract, Sweet Almond Oil, Water, Willow Bark Extract

Questions or comments

info@workvie.com